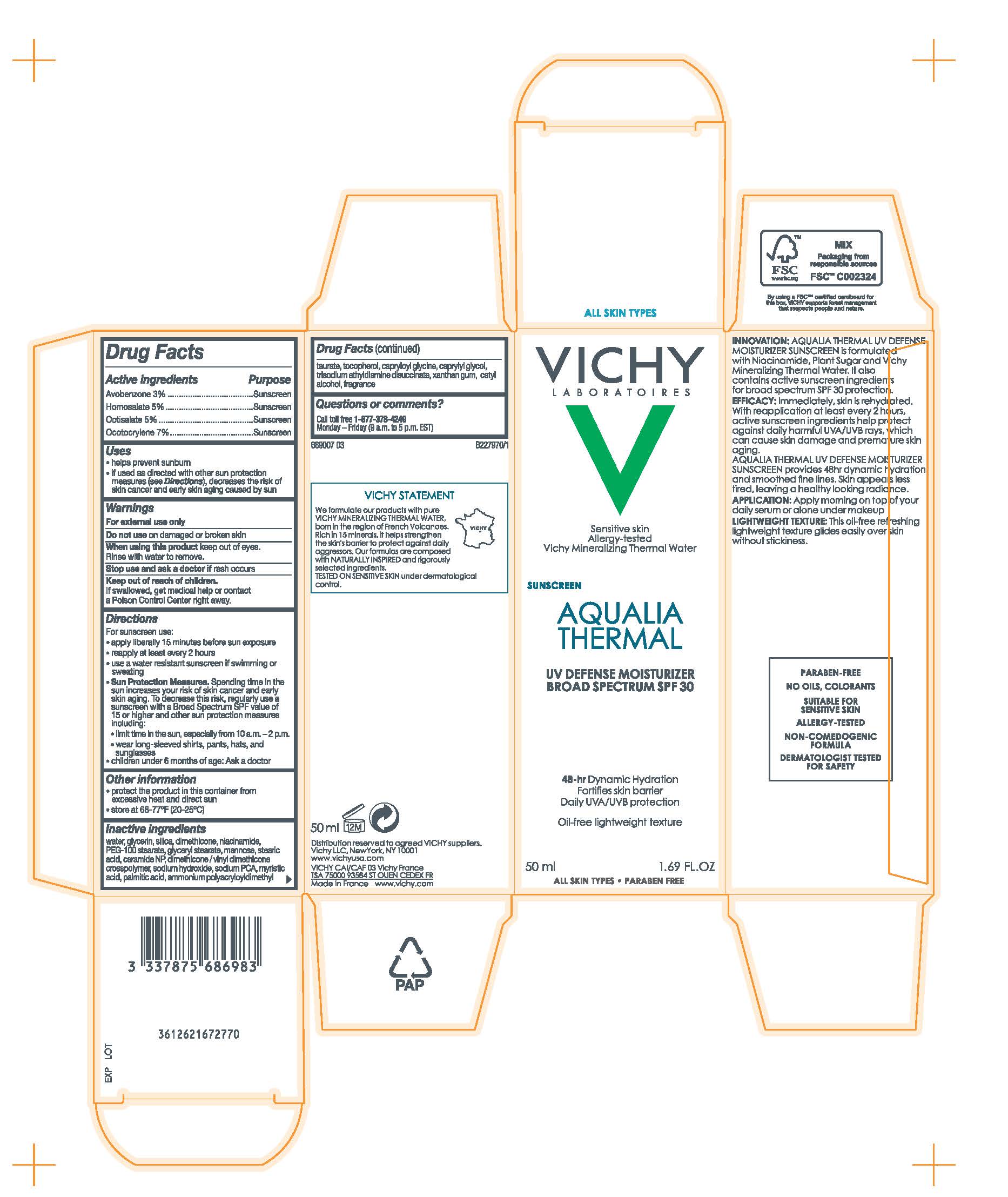 DRUG LABEL: Vichy Laboratoires Aqualia Thermal UV Defense Broad Spectrum SPF 30 Sunscreen
NDC: 69625-868 | Form: Lotion
Manufacturer: Cosmetique Active Production
Category: otc | Type: HUMAN OTC DRUG LABEL
Date: 20241228

ACTIVE INGREDIENTS: AVOBENZONE 30 mg/1 mL; HOMOSALATE 50 mg/1 mL; OCTISALATE 50 mg/1 mL; OCTOCRYLENE 70 mg/1 mL
INACTIVE INGREDIENTS: WATER; GLYCERIN; SILICON DIOXIDE; DIMETHICONE; NIACINAMIDE; PEG-100 STEARATE; GLYCERYL MONOSTEARATE; MANNOSE, D-; STEARIC ACID; CERAMIDE NP; DIMETHICONE/VINYL DIMETHICONE CROSSPOLYMER (SOFT PARTICLE); SODIUM HYDROXIDE; SODIUM PYRROLIDONE CARBOXYLATE; MYRISTIC ACID; PALMITIC ACID; AMMONIUM POLYACRYLOYLDIMETHYL TAURATE (55000 MPA.S); TOCOPHEROL; CAPRYLOYL GLYCINE; CAPRYLYL GLYCOL; TRISODIUM ETHYLENEDIAMINE DISUCCINATE; XANTHAN GUM; CETYL ALCOHOL

Drug Facts

Active ingredients

Avobenzone 3%

Homosalate 5%

Octisalate 5%

Octocrylene 7%

Purpose

Sunscreen

Uses

- helps prevent sunburn
- if used as directed with other sun protection measures (see Directions), decreases the risk of skin cancer and early skin aging caused by the sun

Warnings

For external use only

Keep out of reach of children.

If swallowed, get medical help or contact a Poison Control Center right away.

Do not use

on damaged or broken skin

When using this product

keep out of eyes. Rinse with water to remove.

Stop use and ask a doctor if

rash occurs

Directions

For sunscreen use:

● apply liberally 15 minutes before sun exposure

● reapply at least every 2 hours

● use a water resistant sunscreen if swimming or sweating

● Sun Protection Measures. Spending time in the sun increases your risk of skin cancer and early skin aging. To decrease this risk, regularly use a sunscreen with a Broad Spectrum SPF value of 15 or higher and other sun protection measures including:

● limit time in the sun, especially from 10 a.m. – 2 p.m.

● wear long-sleeved shirts, pants, hats, and sunglasses

● children under 6 months of age: Ask a doctor

Other information

protect the product in this container from excessive heat and direct sun

Inactive ingredients

water, glycerin, silica, dimethicone, niacinamide, PEG-100 stearate, glyceryl stearate, mannose, stearic acid, ceramide NP, dimethicone/vinyl dimethicone crosspolymer, sodium hydroxide, sodium PCA, myristic acid, palmitic acid, ammonium polyacryloyldimethyl taurate, tocopherol, capryloyl glycine, caprylyl glycol, trisodium ethylenediamine disuccinate, xanthan gum, cetyl alcohol, fragrance

Questions or comments?

Call toll free 1-877-378-4249

Monday - Friday (9 a.m. - 5 p.m. EST)